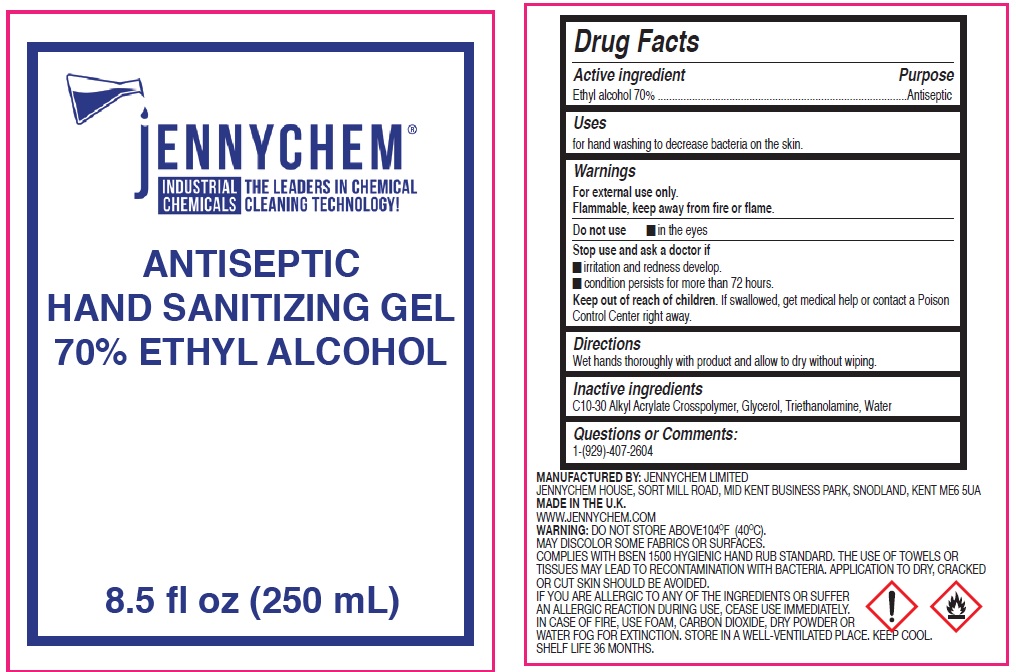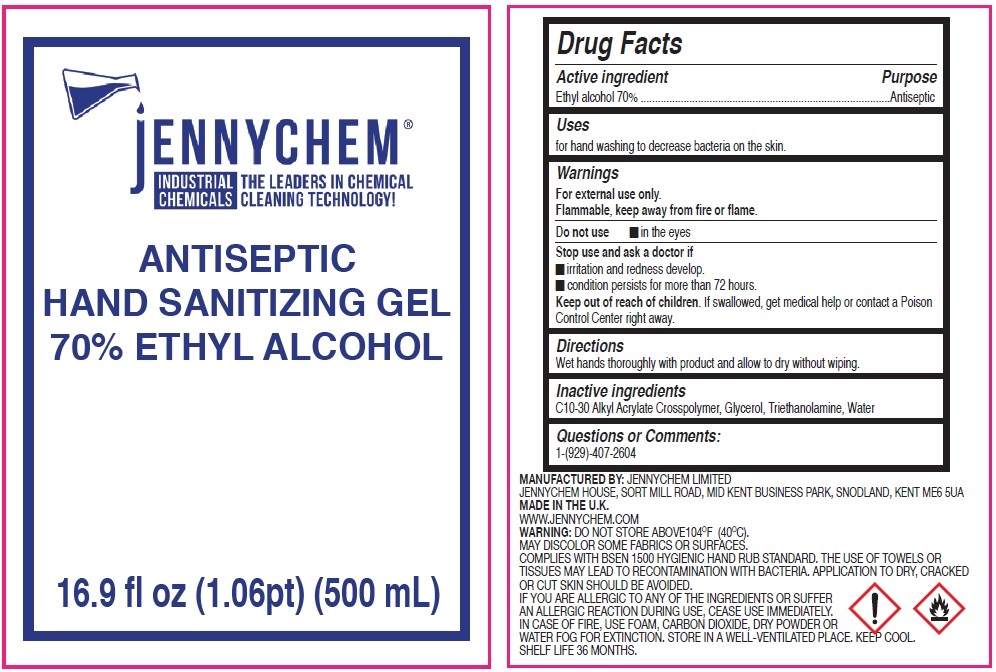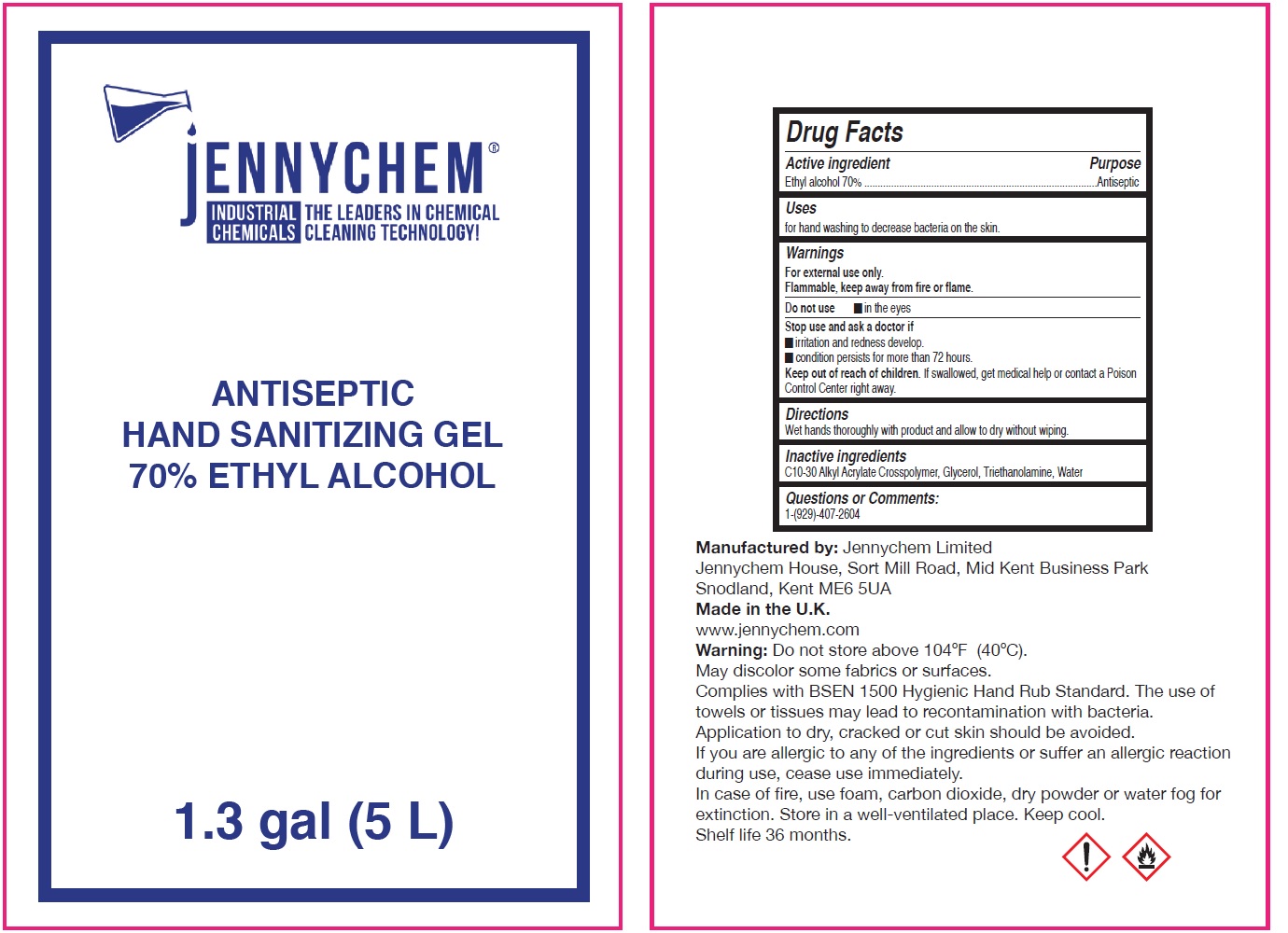 DRUG LABEL: Antiseptic Hand Sanitizing Gel
NDC: 79700-000 | Form: GEL
Manufacturer: Jennychem Limited
Category: otc | Type: HUMAN OTC DRUG LABEL
Date: 20200828

ACTIVE INGREDIENTS: ALCOHOL 0.7 mL/1 mL
INACTIVE INGREDIENTS: CARBOMER INTERPOLYMER TYPE A (ALLYL SUCROSE CROSSLINKED); GLYCERIN; TROLAMINE; WATER

Antiseptic Hand Sanitizing Gel 70% Ethyl Alcohol

Active ingredient

Ethyl alcohol 70%

Purpose

Antiseptic

Uses

for hand washing to decrease bacteria on the skin.

Warnings

For external use only.

Flammable, keep away from fire or flame.

Do not use

- in the eyes

Stop use and ask a doctor if

- irritation and redness develop.
- condition persists for more than 72 hours.

Keep out of reach of children.

If swallowed, get medical help or contact a Poison Control Center right away.

Directions

Wet hands thoroughly with product and allow to dry without wiping.

Inactive ingredients

C10-30 Alkyl Acrylate Crosspolymer, Glycerol, Triethanolamine, Water

Questions or Comments:

1-(929)-407-2604